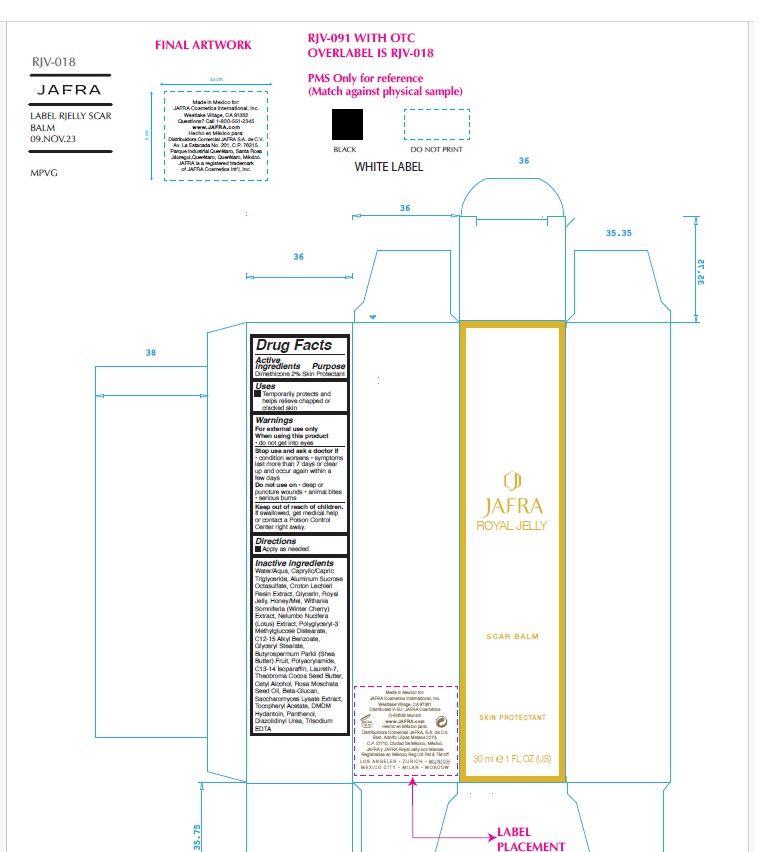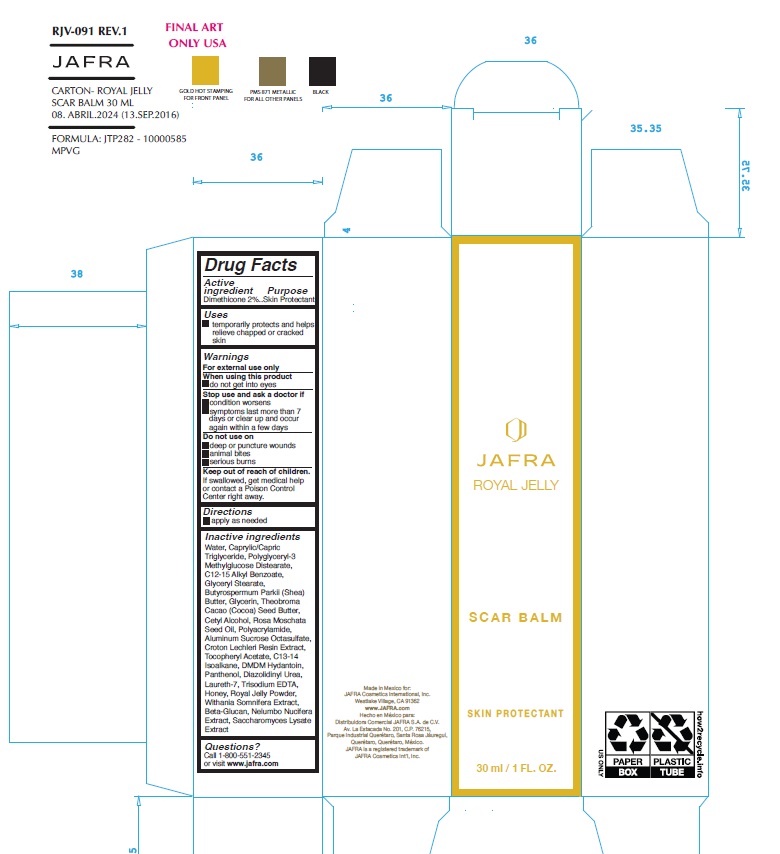 DRUG LABEL: Royal Jelly Scar Balm
NDC: 68828-004 | Form: CREAM
Manufacturer: Distribuidora Comercial Jafra, S.A. de C.V.
Category: otc | Type: HUMAN OTC DRUG LABEL
Date: 20250102

ACTIVE INGREDIENTS: DIMETHICONE 2 g/100 mL
INACTIVE INGREDIENTS: WATER; MEDIUM-CHAIN TRIGLYCERIDES; SUCRALFATE; CROTON LECHLERI RESIN; GLYCERIN; ROYAL JELLY; HONEY; WITHANIA SOMNIFERA FLOWER; NELUMBO NUCIFERA WHOLE; POLYGLYCERYL-3 METHYLGLUCOSE DISTEARATE; ALKYL (C12-15) BENZOATE; GLYCERYL MONOSTEARATE; SHEA BUTTER; POLYACRYLAMIDE (1500 MW); C13-14 ISOPARAFFIN; LAURETH-7; COCOA BUTTER; CETYL ALCOHOL; ROSA MOSCHATA SEED OIL; YEAST .BETA.-D-GLUCAN; SACCHAROMYCES LYSATE; .ALPHA.-TOCOPHEROL ACETATE; DMDM HYDANTOIN; PANTHENOL; DIAZOLIDINYL UREA; EDETATE TRISODIUM

Active ingredient

Dimethicone 2%

Purpose

Skin protectant

Uses

Temporarily protects and helps relieve chapped or cracked skin

Warning

For external use only
When using this product● do not get into eyes
Stop use and ask a doctor if ● condition worsens ● symptoms last more than 7 days or clear up and occur again in a few days
Do not use on● deep or puncture wounds ● animal bites ● serious burns
Keep out of reach of children. If swallowed, get medical help or contact a Poison Control Center right away.

Directions

• apply as needed

Inactive ingredients

Water, Caprylic/Capric Triglyceride, Polyglyceryl-3 Methylglucose Distearate, C12-15 Alkyl Benzoate, Glyceryl Stearate, Butyrospermum Parkii (Shea) Butter, Glycerin, Theobroma Cacao (Cocoa) Seed Butter, Cetyl Alcohol, Rosa Moschata Seed Oil, Polyacrylamide, Aluminum Sucrose Octasulfate, Croton Lechleri Resin Extract, Tocopheryl Acetate, C13-14 Isoalkane, DMDM Hydantoin, Panthenol, Diazolidinyl Urea, Laureth-7, Trisodium EDTA, Honey, Royal Jelly Powder, Withania Somnifera Extract, Beta-Glucan, Nelumbo Nucifera Extract, Saccharomyces Lysate Extract

Questions?Call 1-800-551-2345 or visit www.jafra.com